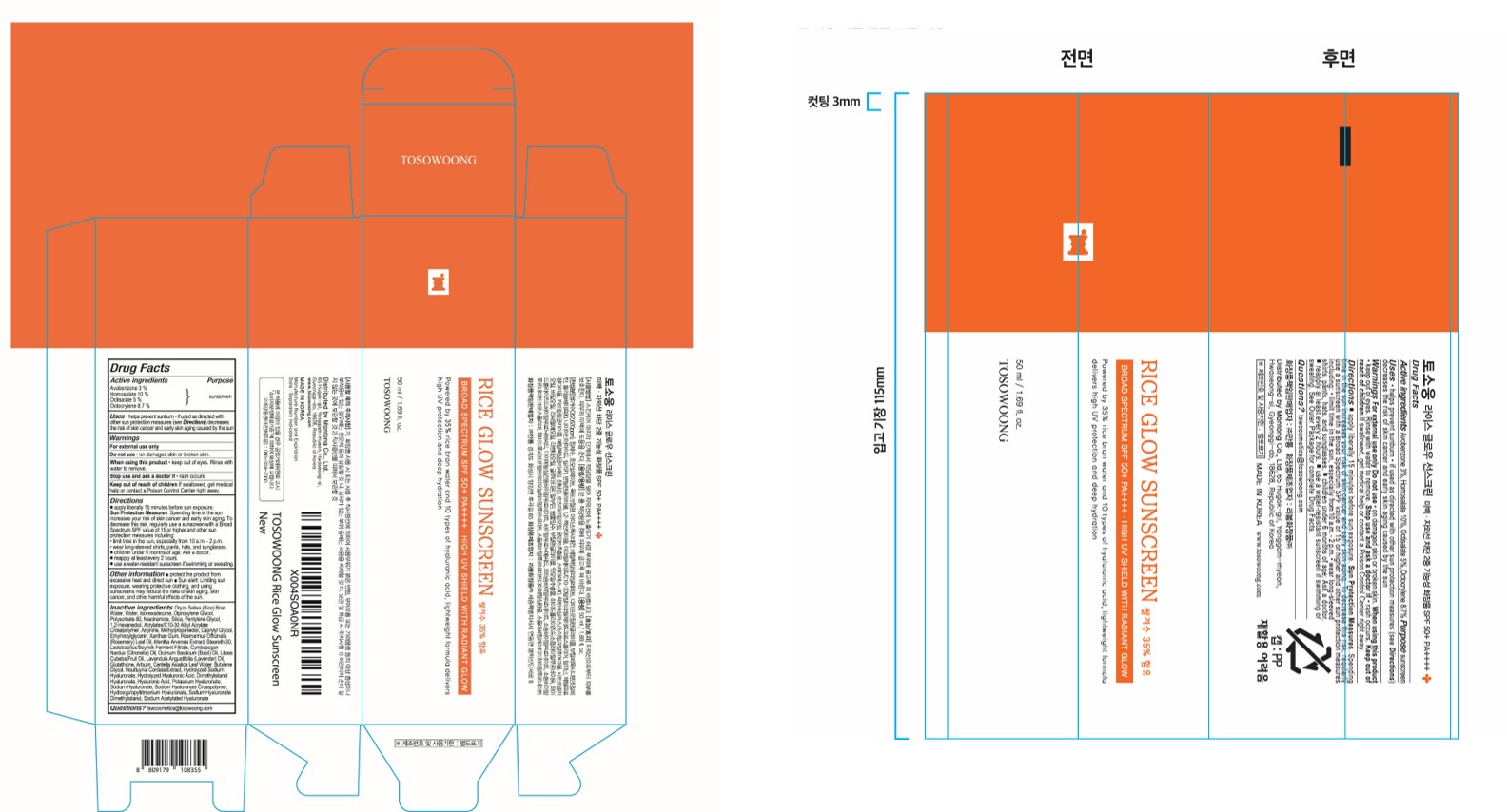 DRUG LABEL: TOSOWOONG Rice Glow SunScreen
NDC: 87017-001 | Form: CREAM
Manufacturer: MANTONG Co., Ltd.
Category: otc | Type: HUMAN OTC DRUG LABEL
Date: 20251021

ACTIVE INGREDIENTS: OCTOCRYLENE 4.35 g/50 mL; AVOBENZONE 1.5 g/50 mL; OCTISALATE 2.5 g/50 mL; HOMOSALATE 5 g/50 mL
INACTIVE INGREDIENTS: RICE BRAN, DEFATTED; 1,2-HEXANEDIOL; CAPRYLYL GLYCOL; ISOHEXADECANE; POLYSORBATE 80; CYMBOPOGON NARDUS (CITRONELLA) OIL; XANTHAN GUM; ETHYLHEXYLGLYCERIN; DIMETHYLSILANOL HYALURONATE; HYALURONIC ACID; SODIUM HYALURONATE; ROSMARINUS OFFICINALIS (ROSEMARY) LEAF OIL; NIACINAMIDE; OCIMUM BASILICUM (BASIL) OIL; BUTYLENE GLYCOL; WATER; METHYLPROPANEDIOL; LAVANDULA ANGUSTIFOLIA (LAVENDER) OIL; HOUTTUYNIA CORDATA FLOWERING TOP; SODIUM ACETYLATED HYALURONATE; ARBUTIN; LITSEA CUBEBA FRUIT OIL; GLUTATHIONE; STEARETH-30; DIPROPYLENE GLYCOL; SILICA; PENTYLENE GLYCOL; ARGININE

TOSOWOONG Rice Glow SunScreen

Active Ingredient

Avobenzone 3 %
Homosalate 10 %
Octisalate 5 %
Octocrylene 8.7 %

Purpose

sunscreen

Uses

helps prevent sunburn • if used as directed with other sun protection measures (see Directions) decreases the risk of skin cancer and early skin aging caused by the sun

Warnings

For external use only

Do no use

• on damaged skin or broken skin

When using this product

• keep out of eyes. Rinse with water to remove.

Stop use ans ask a doctor if

• rash occurs

Keep out of reach of children

If swallowed, get medical help or contact a Poison Control Center right away.

Directions

■ apply liberally 15 minutes before sun exposure.

Sun Protection Measures. Spending time in the sun increases your risk of skin cancer and early skin aging. To decrease this risk, regularly use a sunscreen with a Broad Spectrum SPF value of 15 or higher and other sun protection measures including:

• limit time in the sun, especially from 10 a.m. - 2 p.m.

• wear long-sleeved shirts, pants, hats, and sunglasses

■ children under 6 months of age: Ask a doctor

■ reapply at least every 2 hours

■ use a water-resistant sunscreen if swimming or sweating

Other information

■ protect the product from excessive heat and direct sun ■ Sun alert: Limiting sun exposure, wearing protective clothing, and using sunscreens may reduce the risks of skin aging, skin cancer, and other harmful effects of the sun.

Inactive Ingredients

Oryza Sativa (Rice) Bran Water, Water, Isohexadecane, Dipropylene Glycol, Polysorbate 80, Niacinamide, Silica, Pentylene Glycol, 1,2-Hexanediol, Arginine, Methylpropanediol, Caprylyl Glycol, Ethylhexylglycerin, Xanthan Gum, Rosmarinus Officinalis (Rosemary) Leaf Oil, Steareth-30, Cymbopogon Nardus (Citronella) Oil, Ocimum Basilicum (Basil) Oil, Litsea Cubeba Fruit Oil, Lavandula Angustifolia (Lavender) Oil, Glutathione, Arbutin, Butylene Glycol, Houttuynia Cordata Extract, Dimethylsilanol Hyaluronate, Hyaluronic Acid, Sodium Hyaluronate, Sodium Acetylated Hyaluronate, Acrylates/C10-30 Alkyl Acrylate Crosspolymer, Mentha Arvensis Extract, Lactobacillus/Soymilk Ferment Filtrate, Centella Asiatica Leaf Water, Hydrolyzed Sodium Hyaluronate, Hydrolyzed Hyaluronic Acid, Potassium Hyaluronate, Sodium Hyaluronate Crosspolymer, Hydroxypropyltrimonium Hyaluronate, Sodium Hyaluronate Dimethylsilanol